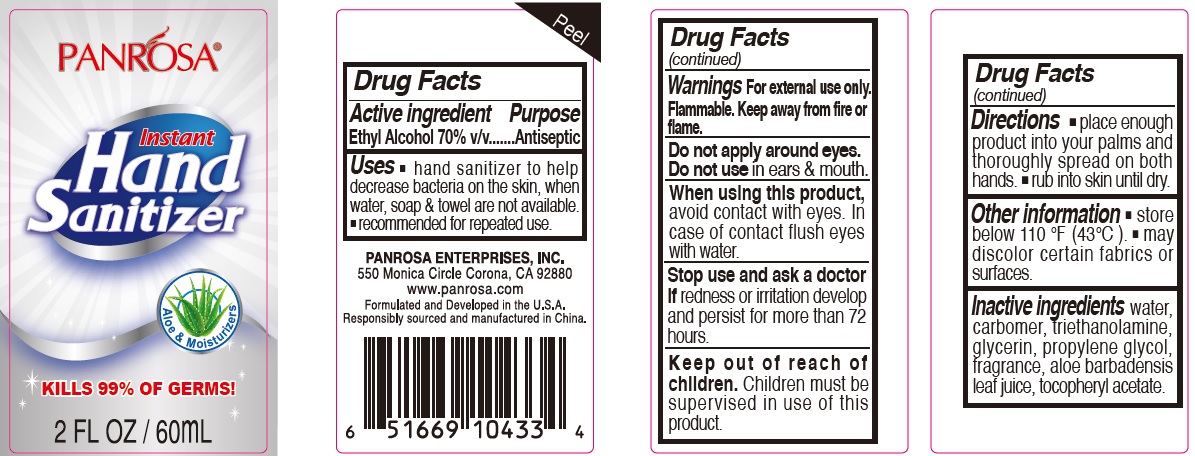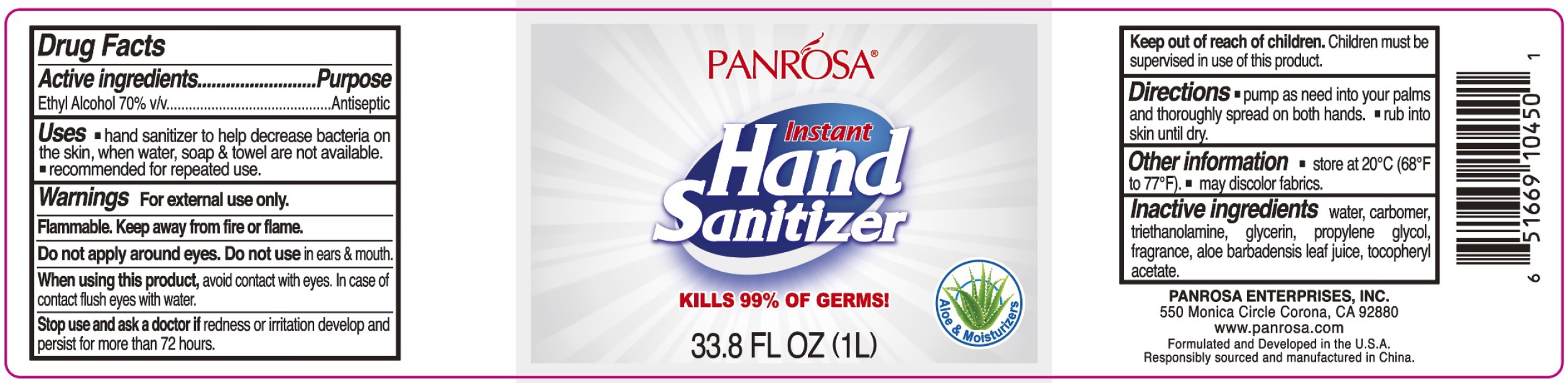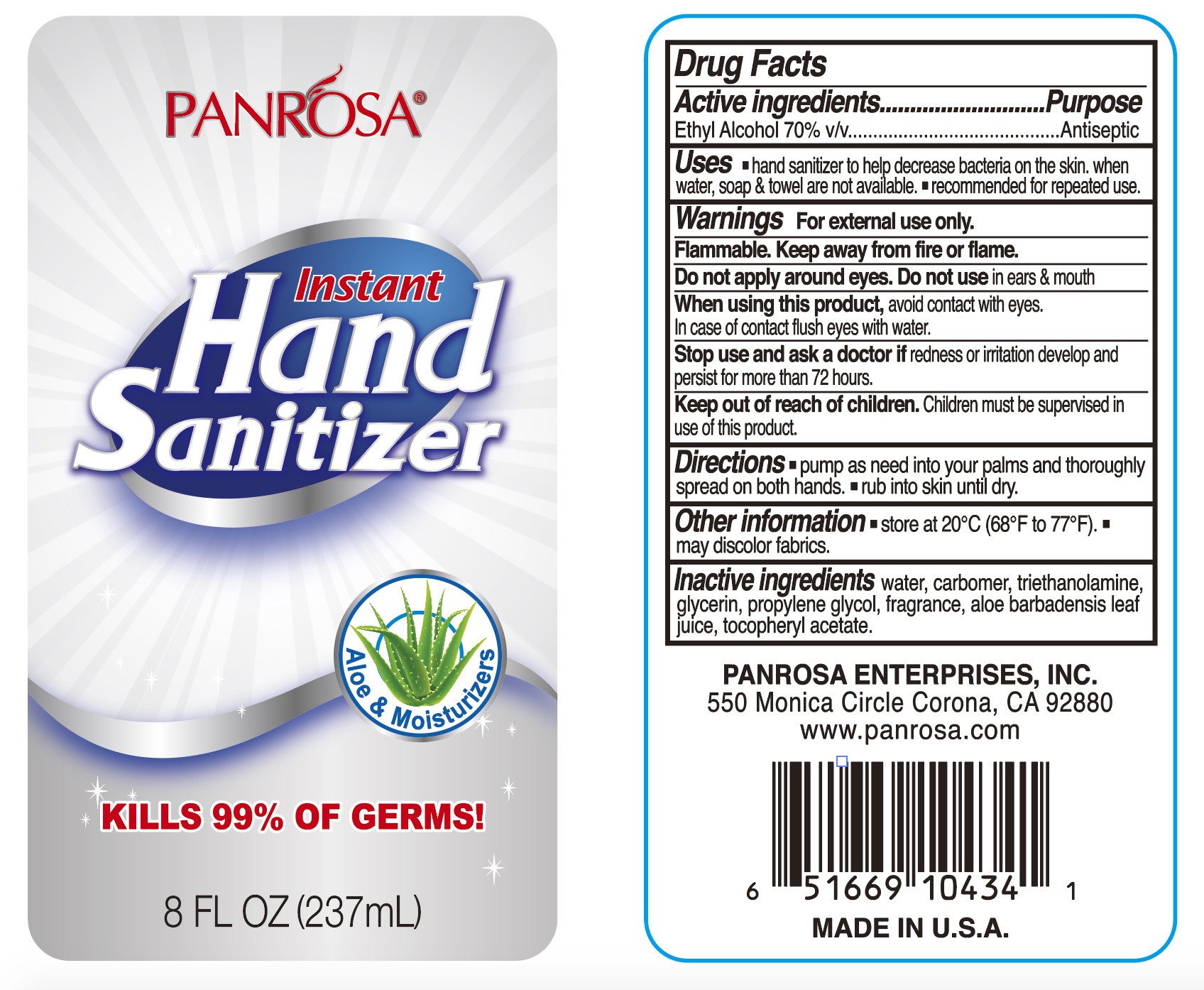 DRUG LABEL: PANROSA Instant Hand Sanitizer Clear
NDC: 50302-003 | Form: GEL
Manufacturer: PANROSA ENTERPRISES, INC.
Category: otc | Type: HUMAN OTC DRUG LABEL
Date: 20211020

ACTIVE INGREDIENTS: ALCOHOL 70 mL/100 mL
INACTIVE INGREDIENTS: WATER; CARBOMER HOMOPOLYMER, UNSPECIFIED TYPE; TROLAMINE; GLYCERIN; PROPYLENE GLYCOL; ALOE VERA LEAF; .ALPHA.-TOCOPHEROL ACETATE

PANROSA Instant Hand Sanitizer Clear

Active ingredients

Ethyl Alcohol 70% v/v

Purpose

Antiseptic

Uses

- hand sanitizer to help decrease bacteria on the skin. when water, soap & towel are not available.
- recommended for repeated use.

Warnings

For external use only.

Flammable. Keep away from fire or flame.

Do not apply around eyes.

Do not use

in ears & mouth

When using this product.

avoid contact with eyes. In case of contact flush eyes with water.

Stop use and ask a doctor if

redness or irritation develop and persist for more than 72 hours.

Keep out of reach of children.

Children must be supervised in use of this product.

Directions

- pump as need into your palms and thoroughly spread on both hands.
- rub into skin until dry.

Other information

- store at 20°C (68°F to 77°F).
- may discolor fabrics.

Inactive ingredients

water, carbomer, triethanolamine, glycerin, propylene glycol, fragrace, aloe barbadensis leaf juice, tocopheryl acetate